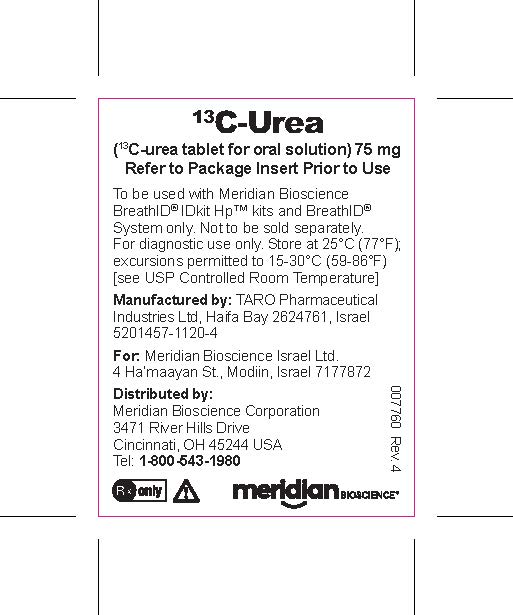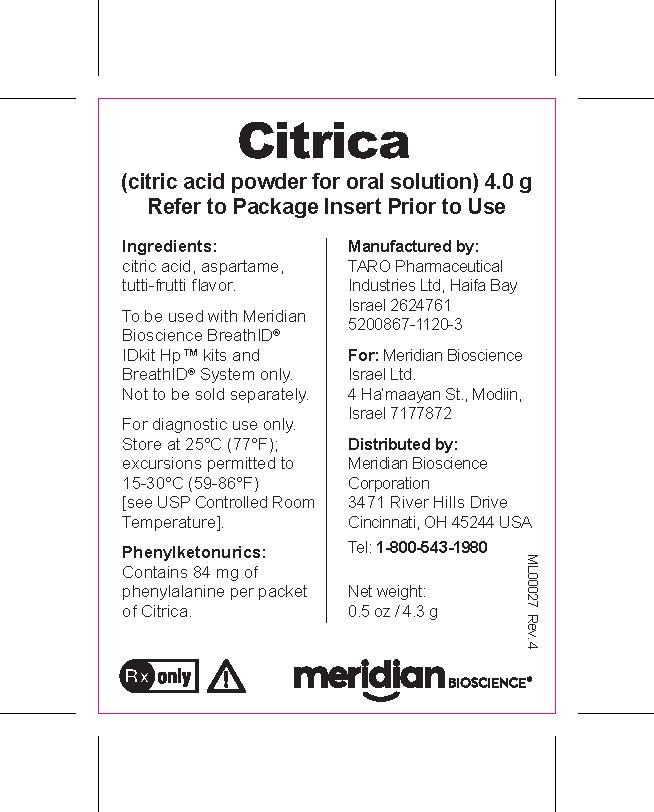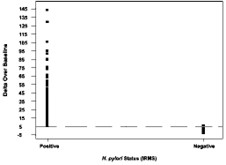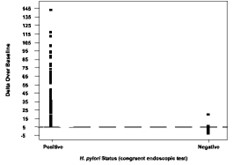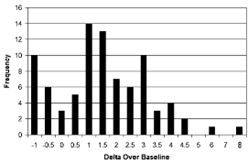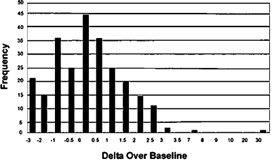 DRUG LABEL: IDkit HP ONE
NDC: 50402-100 | Form: SOLUTION
Manufacturer: Meridian Bioscience Israel Ltd
Category: prescription | Type: HUMAN PRESCRIPTION DRUG LABEL
Date: 20250130

ACTIVE INGREDIENTS: UREA C-13 75 mg/1 1; CITRIC ACID MONOHYDRATE 4 g/1 1

IDkit Hp® Package Insert

Package Insert IDkit Hp® Two for BreathID® Hp Lab System and BreathID® Smart System Breath Test for Detection of H. pylori

SECTION 1. PACKAGE INSERT This package insert includes information for conducting the H. pylori test using the BreathID® Hp Lab System or the BreathID® Smart System for analysis with the Breath Test Kit, IDkit Hp® Two. The following are trademarks of Meridian Bioscience Israel Ltd.: Meridian®, MCS™, IDkit Hp® and BreathID®. All reference to Meridian in this document refers to the company Meridian Bioscience Israel Ltd.

Note: No license, expressed or implied, is granted under any patents of Meridian Bioscience Israel Ltd.

Caution: U.S. Federal Law restricts this device to sale by or on the order of a physician.

SECTION 2. INTENDED USE

The BreathID® Hp Lab System or the BreathID® Smart System is intended for use to non-invasively measure changes in the ^13CO2/1^2CO2 ratio of exhaled breath, which may be indicative of increased urease production associated with active Helicobacter pylori (H. pylori) infection in the stomach.

The BreathID® Hp Lab System or BreathID® Smart System is indicated for use as an aid in the initial diagnosis and post treatment monitoring of H. pylori infection in adult patients and pediatric patients ages 3-17 years old. The BreathID® Hp Lab System consists of the appropriate IDkit Hp® kit and the BreathID® Hp device, Auto Sampler and Lab Application. The BreathID® Smart System consists of the appropriate IDkit Hp® kit and the BreathID® Smart device.

To be administered by trained personnel as ordered by a licensed healthcare practitioner.

SECTION 3. SUMMARY AND EXPLANATION

Since the initial identification of H. pylori in the early 1980s [1], the management of upper gastrointestinal disease has changed dramatically. “Helicobacter pylori is now recognized as an important pathogen and a causal relationship between H. pylori and chronic active gastritis, duodenal ulcer, and gastric ulcer is well documented”[2]. Currently there are numerous H. pylori detection technologies for upper gastrointestinal disease including biopsy and serum analysis. These technologies depend on two general approaches for obtaining a sample for testing: invasive and non-invasive. The first invasive test method requires an endoscopic gastric biopsy. The tissue collected from the biopsy is then examined in a laboratory by microbiological culture of the organism, direct detection of urease activity in the tissue, or by histological examination of stained tissue. Biopsy-based methods present an element of patient risk and discomfort and may provide false negative results due to sampling errors. The second invasive test is a serological test; this requires a blood sample which is used to detect serum antibodies to H. pylori. The disadvantage of this test is that it is difficult to distinguish between positive active infections and past exposure to infection, and therefore it is not a conclusive indicator of current H. pylori infection. ^13C-urea breath tests provide a non-invasive and non-hazardous analysis of the exhaled breath. The BreathID® test (described in the next section) measures the ^12CO2 and ^13CO2 components of the exhaled breath before and after the oral ingestion of ^13C-enriched urea. This establishes the baseline ratio of ^13CO2/^12CO2 and the post ingestion ratio of ^13CO2/^12CO2 in order to determine the Delta Over Baseline[1] (change in the ^13CO2/^12CO2 ratio).

SECTION 4. PRINCIPLES OF THE BREATHID® BREATH TEST

The BreathID® non-invasive breath test is a diagnostic test that analyzes a breath sample before and after ingestion of ^13C-enriched urea; it is used to identify those patients with H. pylori infection. The BreathID® breath test is performed as follows: a 75 mg ^13C-urea tablet and 4.3 g Citrica Powder are dissolved in water, and the resulting solution is ingested by the patient. The presence of the Citrica creates an acidic environment in the stomach and also delays the transfer of the ingested solution to the duodenum. These two characteristics facilitate the decomposition of the urea by H. pylori, if present. Thus, in the presence of urease associated with gastric H. pylori, ^13C-urea is decomposed to ^13CO2 and NH3 according to the following equation:

H. pylori urease

2 ^13C-urea + 2 H2O →→→→→→→→→→ 2 ^13CO2 + 2 NH3

The ^13CO2 is absorbed into the blood and then exhaled in the breath. Absorption and distribution of ^13CO2 is fast. Therefore, the cleavage of urea by the H. pylori urease that produces the 13CO2 occurs immediately after the solution is ingested and enables immediate detection of increased ^13CO2 in the exhaled breath of H. pylori-positive patients. In the case of H. pylori-negative patients, the ^13C-urea does not produce ^13CO2 in the stomach because there are no human enzymes that can decompose the urea in the stomach.

4.1. DESCRIPTION OF THE MODE OF OPERATION OF THE BREATHID® HP LAB AND BREATHID® SMART DEVICES

The test consists of two phases, the Sampling phase, at which time two Breath Sample Bags are inflated by the patient, and the Analysis phase as which time the two Breath Sample Bags are analyzed together using the BreathID® Hp Lab System or the BreathID® Smart System.

Sampling phase begins with the collection of a baseline breath sample. The patient inflates the Baseline Breath Sample Bag. The patient then ingests a test drink consisting of ^13C-urea tablet 75mg and 4.3g of Citrica Powder (4g citric acid). After 15-20 minutes a post-ingestion sample is collected by inflation of the Post Ingestion Breath Sample Bag. The analysis is performed with the BreathID® System up to 14 days from sample collection, either locally or remotely. The ^13CO2/^12CO2 ratio is measured and the DOB computed.

Delta Over Baseline is defined as: { (^13CO2(n)/^12CO2(n) - ^13CO2(0)/ ^12CO2(0))*1000}/ (^13CO2(PDB)/^12CO2(PDB)) where PDB is the standard ^13C/^12C isotope ratio (=1.1273%). (0) is the baseline measurement and (n) is the measurement of interest.

SECTION 5. REAGENT

5.1. ^13C-UREA DIAGNOSTIC COMPONENT DESCRIPTION

The diagnostic drug component of the kit is ^13C-enriched urea prepared as a tablet. The tablet should be dissolved with Citrica Powder in a glass of water, providing a clear, colorless solution for oral administration. The 75mg ^13C-urea component is supplied as a tablet in a sealed pouch. The 4.3g of Citrica Powder (4g citric acid, [3,4,5], aspartame, and Tutti Frutti flavoring) is supplied in a separate sealed pouch. An average adult body normally contains about 9.0 grams of urea, which is a product of protein metabolism. Urea in the body is referred to as a natural isotopic abundance urea since it is composed of 98.9% ^12C-urea and 1.1% ^13C-urea. Greater than or equal to 99% of the carbon molecules in the supplied tablet are in the form of ^13C; a stable, naturally occurring, non-radioactive isotope of carbon. ^13C-urea is the diamide of ^13C carbonic acid and is highly soluble in water (1 gram per ml at 25°C). It has the following chemical formula: ^13CH4N2O.

5.2 WARNINGS AND PRECAUTIONS

1. For in vitro diagnostic use only. The ^13C-urea tablet and Citrica Powder are dissolved in a glass of water and the resulting solution is taken orally as part of the diagnostic procedure.

2. Phenylketonurics: Contains Phenylalanine, 84 mg per dosage unit of Citrica Powder.

3. In the case of accidental overdose – drink water and call the physician.

4. A negative result does not rule out the possibility of H. pylori infection. False negative results can occur with this procedure. If clinical signs suggest H. pylori infection, retest with a new sample or an alternate method.

5. A false positive test may occur due to urease associated with other gastric spiral organisms observed in humans such as Helicobacter heilmanni.

6. A false positive test could occur in patients who have achlorhydria.

7. False negative test results may be caused by:
• Ingestion of antimicrobials or bismuth preparations within two weeks prior to performing the breath test.
• Ingestion of proton pump inhibitors (PPIs) within two weeks prior to performing the breath test.
Note: If a negative result is obtained from a patient ingesting a PPI within two weeks prior to the breath test, the results cannot be considered indicative of the absence of urease associated with H. pylori and the test should be repeated two weeks after discontinuing the PPI treatment. A positive result for a patient on a PPI could be considered as indicative of the presence of urease associated with H. pylori.

8. Tiny particles may remain visible in the reconstituted ^13C-urea and Citrica solution after thorough mixing for up to five minutes. However, if more substantial particulate matter is still present after five minutes of mixing, the solution should not be used, and a new kit should be opened.

9. Safety and effectiveness have not been assessed in children below the age of 3 years.

5.3. MIXING THE 13C-UREA TABLET

1. Dissolve the Citrica and the ^13C-enriched urea tablet in 150 to 200 ml (5.1 to 6.8 oz.) of tap water in the provided drinking cup.

2. Close the lid firmly using both hands. Place fingers over lid and shake thoroughly for a few minutes, until the Citrica Powder and the urea tablet are completely dissolved.

Note: Tiny particles may remain visible after thorough mixing. However, if more substantial particulate matter is still present after five minutes of mixing, discard the solution and repeat the procedure with a new kit.

5.4. SHELF LIFE AND STORAGE

Store at 25°C (77°F); excursions permitted to 15-30°C (59-86°F) [see USP Controlled Room Temperature]. The following components of the test kit have expiration dates: the 13C-urea tablet and the Citrica Powder. Do not use either of these components beyond the expiration date stated on the respective labels. The earlier of the two expiry dates appears on the IDkit Hp® Two box.

5.5. PURIFICATION OR TREATMENT Purification or treatment for the ^13C-urea tablet is not required prior to use.

5.6. INSTABILITY OR DETERIORATION There are no known physical, biological, or chemical indications of instability or deterioration for the 13C-urea tablet

SECTION 6. ADVERSE EVENTS

6.1 Following FDA clearance of the IDkit: Hp® One kits (using the identical ^13C-urea tablet and Citrica powder), the following adverse events have been identified: anaphylactic reaction, diarrhea and vomiting. Because these reactions are reported voluntarily from a population of uncertain size, it is not always possible to establish a causal relationship to drug exposure.

6.2 In two clinical studies conducted in 465 patients’ of at least 18 years-old and older to determine the initial diagnosis and post treatment monitoring of H. pylori infection using the IDkit Hp® Two kits, the following adverse events experienced by 1.5% of these patients were nausea (0.6%), throat burning (0.4%) and lightheadedness (0.4%). The last one was reported after blowing into the bags. The potential adverse events were experienced by the patients within minutes of ingestion of the ^13C-urea tablet and Citrica powder. In a clinical study conducted in 53 pediatric patients, aged 3 to 17 years, using the IDkit Hp® Two kit one adverse event of vomiting was experienced by one subject (1.89%). It resolved on the same day.

SECTION 7. INSTRUMENTS

The BreathID® non-invasive breath test is a diagnostic test that analyzes a breath sample before and after ingestion of ^13C-enriched urea; it is used to identify those patients with H. pylori infection. The samples need to be tested with the BreathID® Hp Lab System or the BreathID® Smart System. For detailed information on the BreathID® System, reference the Operator's Manual supplied with the BreathID® System.

7.1 USE AND FUNCTION OF BREATHID® HP LAB AND BREATHID® SMART SYSTEMS

The BreathID® Hp Lab System or the BreathID® Smart System is intended for use to non-invasively measure changes in the 13CO2/12CO2 ratio of exhaled breath, which may be indicative of increased urease production associated with active Helicobacter pylori (H. pylori) infection in the stomach.

The BreathID® Hp Lab System or the BreathID® Smart System is indicated for use as an aid in the initial diagnosis and post treatment monitoring of H. pylori infection in adult patients and pediatric patients ages 3-17 years old.

7.2 PRINCIPLE OF OPERATION

The BreathID® breath test is performed as follows: a 75mg ^13C-urea tablet and 4.3g Citrica Powder are dissolved in water and the resulting solution is ingested by the patient. The presence of the Citrica creates an acidic environment in the stomach and also delays the transfer of the ingested solution to the duodenum. These two characteristics facilitate the decomposition of the urea by H. pylori, if present. The ^13CO2 is absorbed into the blood and then exhaled in the breath. Absorption and distribution of ^13CO2 is fast. Therefore, the cleavage of urea by the H. pylori urease that produces the ^13CO2 occurs immediately after the solution is ingested and enables immediate detection of increased ^13CO2 in the exhaled breath of H. pylori-positive patients.

For detailed information on the principle of operation of the BreathID® Breath Test, refer to section 4.

7.3. PERFORMANCE CHARACTERISTICS

Adults

A multi-center, prospective, non-randomized, open label, validation, pivotal study, designed to confirm the efficacy of the IDkit Hp® Two as part of the BreathID® Hp Lab System was performed for initial diagnosis (pre-therapy) and post eradication testing using 5 DOB diagnostic cut-off (see section 10.3) versus composite biopsy results (histology and RUT). The study included a total of 247 consecutive adult subjects evaluable for efficacy per protocol (179 initial diagnosis and 68 post eradication). The following efficacy measures were determined for initial diagnosis:

Sensitivity: 100% x 37/37 = 100% [95% CI (90.60; 100.00)]
Specificity: 100% x 139/142 = 97.9% [95% CI (93.97; 99.28)]

Pediatrics

A multi-center, non-randomized, open label study was conducted with the primary goal of confirming the safety of the 13C-urea substrate in pediatric subjects, and a secondary goal of evaluating performance of the BreathID® Hp Lab System in pediatric subjects with breath collection using IDkit Hp® Two in this population, compared to stool antigen testing. Supported by existing clinical performance in the adult population, device performance was assessed in a limited clinical study in a pediatric population as described below. The study was not powered to assess efficacy in pediatric subjects and the standard reference method (i.e. composite results based on samples from endoscopy) was not used as the comparator method. The study included a total of 53 consecutive pediatric subjects with 42 evaluable for efficacy. The positive percent agreement between the breath test and the stool antigen test results was 93.3% [95% CI:68.05;99.83] and the negative percent agreement was 100% [95% CI: 87.23%;100%].

A detailed description of the performance characteristics of the BreathID® device using IDkit Hp® Two in adult and pediatric patients is provided in section 13.

7.4 OPERATIONAL PRECAUTIONS AND LIMITATIONS

The following precautions and limitations are applicable to the BreathID® Hp Lab System and the BreathID® Smart System:

1. A negative result does not rule out the possibility of H. pylori infection. False negative results can occur with this procedure. If clinical signs suggest H. pylori infection, retest with a new sample or an alternate method.

2. A false positive test may (rarely) occur due to urease associated with other gastric spiral organisms observed in humans such as Helicobacter heilmanni.

3. A false positive test could occur in patients who have achlorhydria.

4. The patient should not have taken antimicrobials, proton pump inhibitors (PPI) or bismuth preparations within two weeks prior to administering the test.

5. If the test is negative and it is determined that the subject has used PPIs within two weeks prior to taking the breath test, the test may provide a false negative result. The test needs to be repeated two weeks post discontinuation of PPI treatment.

6. A positive result for a patient on PPI could be considered as indicative of the presence of urease enzyme associated with H. pylori.

7. Do not clean or sterilize the Breath Sample Bags. The bags are intended for single patient use only.

SECTION 8. SPECIMEN COLLECTION AND PREPARATION

8.1. PATIENT PREPARATION

Remind the patient that the Citrica contains 84mg of phenylalanine per packet of Citrica Powder. Phenylketonurics restrict dietary phenylalanine. The patient should have fasted at least one hour before administering the solution. The patient should not have taken antimicrobials, proton pump inhibitors (PPI) or bismuth preparations within two weeks prior to administering the test. If PPIs are used within two weeks of breath testing, false negative test results may occur, and the test should be repeated two weeks after discontinuation of PPI treatment. A positive result for a patient on PPI could be considered as indicative of the presence of urease enzyme associated with H. pylori.

8.2. ADDITIVES AND PRESERVATIVES

The BreathID® Systems do not require any additives, preservatives, etc. to maintain the integrity of the breath sample.

8.3. INTERFERING SUBSTANCES

Potentially interfering substances typically found in a patient’s breath were tested using the original BreathID® System to determine their effect on the test results. The potential sources tested were:

Mouthwash
Chewing gum
Carbonated beverages
Cigarette smoke
Acetone (to simulate the effect of ketone production that may result from some diets)
Alcohol

There was no observation that these substances had any significant influence on the outcome of the test.

8.4. BREATH SAMPLE HANDLING INSTRUCTIONS

The analysis of the breath samples should be conducted within 14 days after breath collection; the filled Breath Sample Bags should be stored at 15°- 30°C (59°-86°F) protected from direct sunlight or sharp objects. If desired, use the provided sample transport bag for transport of the breath samples.

SECTION 9. PROCEDURE

9.1. MATERIALS

A single BreathID® IDkit Hp® Two is provided to perform the Breath Test. Each IDkit Hp® Two contains:

One package insert
One tablet of ^13C-enriched urea, 75 mg
One packet of 4.3 g (4 g citric acid, aspartame, Tutti Frutti flavoring) of Citrica Powder
One straw for drinking
One drinking cup
One blue BASELINE Breath Sample Bag for BASELINE breath collection prior to ingestion of test substrate
One gray POST INGESTION Breath Sample Bag for 15 minutes POST INGESTION breath collection
One large sample transport bag provided to store/ship both Breath Sample Bags
Four barcode labels (one for each Breath Sample Bag and two for the requisition form)
One Quick User Guide showing the basic steps of administering the test (may be printed on the inside of the box)

Materials Needed But Not Provided:

Tap water
Timer

9.2. STEP-BY-STEP PROCEDURE

For performing the BreathID® H. pylori test, use the IDkit Hp® Two single-use kit.

1. Verify that the patient has been prepared for the breath test as specified in Section 8.

2. Verify that the entire package is intact and contains all the materials listed in Section 9.1.

3. Identify the two Breath Sample Bags (the blue BASELINE bag and the gray POST INGESTION bag).

4. Prior to sampling the patient’s breath, label each bag with the supplied barcode labels or write the necessary identification information in the appropriate fields on each bag.

5. Collection of the BASELINE breath sample:

I. Remove the cap from the mouthpiece of the blue BASELINE bag.

II. Instruct the patient to take a deep breath, hold their breath for 4 to 5 seconds and then exhale directly into the mouthpiece of the blue BASELINE breath bag until completely full.

III. If the bag is not full repeat step II.

IV. Replace the cap on the bag mouthpiece and firmly press until it clicks and is securely locked into place.

Note: If the patient has not held their breath for 4-5 seconds or does not fill the bag completely, there is a possibility a test result will not be obtainable.

Note: The bag is not fully closed if the cap does not click into place. Not fully closing the bag my cause the breath sample to slowly leak out.

6. Preparing the test drink:

Note: Administer the test drink within two hours of preparation, as this is the maximal time for maintaining solution stability.

I. Dissolve the Citrica Powder and the ^13C-enriched urea tablet in 5.1 to 6.8 oz. (150 to 200 ml) of tap water in the provided drinking cup.

II. Close the lid firmly using both hands. Place fingers over lid and shake thoroughly for a few minutes, until the Citrica Powder and the 13C-urea tablet are completely dissolved.

Note: Tiny particles may remain visible after thorough mixing. However, if more substantial particulate matter is still present after five minutes of mixing, discard the solution and repeat the procedure with a new kit.

7. Administering the test drink:

I. Give the prepared test drink to the patient.

II. Ensure that the patient drinks the solution through the provided straw.

III. The patient, including pediatric patients aged 3-17 regardless of age and bodyweight, must drink the solution within two minutes and consume the entire amount.

IV. Start the timer for 15 minutes.

V. After the patient finishes drinking the solution, record the present time plus (+) another 15 minutes in the Time to Fill field on the gray POST INGESTION bag.

8. Collection of the POST INGESTION breath sample:

I. Fifteen minutes after the administration of the test drink (but not later than 20 minutes after administration) remove the cap from the mouthpiece of the gray POST INGESTION bag.

II. Instruct the patient to take a deep breath, hold their breath for 4 to 5 seconds and then exhale directly into the mouthpiece of the gray POST INGESTION bag until it is full.

III. If the bag is not full repeat step II.

IV. Replace the cap on the bag mouthpiece and firmly press until it clicks and is securely locked into place.

Note: If the patient has not held their breath for 4-5 seconds or does not fill the bag completely, there is a possibility a test result will not be obtainable.

Note: The bag is not fully closed if the cap does not click into place. Not fully closing the bag my cause the breath sample to slowly leak out.

9. Storage of Breath Sample Bags for future measurement:

I. Assure both filled Breath Sample Bags are correctly labeled and all fields are complete for future identification.

II. Place both filled Breath Sample Bags (the blue BASELINE bag and the gray POST INGESTION bag) into the provided sample transport bag.

III. Until analyzed, Breath Sample Bags should be stored at room temperature (15-30°C, 59-86°F), protected from direct sunlight and sharp objects. Refrain from applying any external pressure on the Breath Sample Bags.
A BreathID® Hp Lab System or BreathID® Smart System should be used in order to measure the filled Breath Sample Bags. For more detailed information regarding the step-by-step procedure and device operation, refer to the BreathID® relevant Operator's Manual.

9.3. CALIBRATION

The calibration stability of the BreathID® System is ensured by the Meridian proprietary 12CO2 and 13CO2 Isotope Specific Infrared (ISIR) lamps. The physical process underlying gas discharge emissions supports this stability. The emissions are caused by molecular rotation-vibration transitions, each generating a spectral line at a specific wavelength, uniquely defined to an accuracy of better than 0.01 Å (Angstrom). Five gas samples of known concentration and isotope ratio are used to adjust the absorption cell calibration curves, aiming to attain identical isotope ratios over the collection range of CO2 concentrations. This will ensure accurate readings in both negative and positive samples. In addition, quality checks as described below in section 9.4 are performed automatically by the BreathID® device every 60 days in order to ensure the system performs within established limits, and calibration is performed if required.

9.4. QUALITY CONTROL

The BreathID® Systems undergo rigorous quality assurance procedures before leaving the manufacturer. However, to ensure correct functioning of the system in the field, the BreathID® System will automatically perform a Calibration Check every 60 days. This procedure confirms that the system is functional and is performing within specifications. Complete operating information including appropriate quality control activities is provided in the BreathID® System Operator's Manual. Additionally, each laboratory should follow its internal procedures for quality control.

SECTION 10. TEST RESULTS

10.1. THE TEST METHOD

The ratio of 13CO2 to 12CO2 in breath samples is determined by Molecular Correlation Spectrometry (MCS™), which is utilized by the BreathID® device software.

10.2. CALCULATION OF RESULTS

The results are provided as Delta Over Baseline. Delta Over Baseline is the difference between the Delta values (based on a ratio of 13CO2/12CO2) in the POST INGESTION Breath Sample Bag specimen and the corresponding BASELINE Breath Sample Bag specimen. There are no calculations required by the user.

10.3. DETERMINATION OF THE CUTOFF POINT

The cutoff point is the level (threshold) used to discriminate between H. pylori-infected and uninfected individuals. The Delta Over Baseline cutoff point was determined to be five in a controlled study of 186 adult asymptomatic and symptomatic patients (101 infected and 85 uninfected). The study was conducted in Israel using a local reference standard called the Isotope Ratio Mass Spectrometer (IRMS). The cutoff point was evaluated by determining the original BreathID® test result (DOB) threshold at which positive and negative patients, as determined by the Isotope Ratio Mass Spectrometer, were best distinguished.

Figure 1 shows the BreathID® test cutoff point graphically, which distinguishes H. pylori-positive and negative patients.

Figure 1: Cutoff for BreathID® Test as Determined in an Initial Clinical Study

The cutoff point was confirmed in a controlled pivotal clinical study where 300 subjects were enrolled. The study consisted of a pre-therapy and post-therapy phase. Patients enrolled in the pre-therapy phase had dyspeptic symptoms, active peptic ulcer disease, or a past history of peptic ulcer disease. To be eligible for the post-therapy phase, H. pylori-positive patients had to be treated for infection four weeks prior to enrollment (some patients participated in both the pre-therapy and post-therapy phases). In the pre-therapy phase, 47 patients were found to be infected and 253 were found to be uninfected. Congruent results obtained by rapid urease test and histological examination of biopsy tissue were used as the reference standard. In the post-therapy phase, 22 patients were infected and 50 were uninfected. The reference standard was a positive finding by endoscopic test (rapid urease or histology) or urea breath test (UBT). For more details, refer to section13. In another study the method of breath sampling using breath sample bags was validated comparing to the gold standard (i.e., congruent biopsy results) using the same cutoff.

Figure 2 shows the original BreathID® Delta Over Baseline results.

Figure 2: Cutoff Point for BreathID® Test as Determined for Pre-Therapy Patients in the Pivotal Study

10.4. INTERPRETATION OF RESULTS

A BreathID® test result of greater than 5 Delta Over Baseline is interpreted as diagnostically positive, indicating the presence of urease associated with H. pylori. A BreathID® test result of less than or equal to 5 Delta Over Baseline is interpreted as diagnostically negative, indicating the absence of urease associated with H. pylori. The 5 Delta Over Baseline cutoff point applies to both initial diagnosis and post treatment monitoring of H. pylori infection in adult and pediatric patients. For more details, refer to section 13.

SECTION 11. LIMITATIONS OF THE TEST

1. Post treatment monitoring of H. pylori should be performed after at least six weeks of treatment for H. pylori infection. Earlier assessment may give false results.
2. Safety and effectiveness in patients under the age of 3 years have not been established.
3. Data is insufficient for recommending the use of this test on patients with total or partial gastrectomy.
4. Data is insufficient to recommend the use of this test on pregnant and lactating women.
5. A correlation between the number of H. pylori organisms in the stomach and the BreathID® test results has not been established.

SECTION 12. EXPECTED VALUES

Delta Over Baseline values for the original BreathID® test were determined in a controlled clinical study of 186 adult asymptomatic and symptomatic patients (101 infected and 85 uninfected) in Israel, using a known reference standard called the Isotope Ratio Mass Spectrometer (IRMS) and performed in a local Israeli laboratory. The range of Delta Over Baseline values for the uninfected patients was determined to be between ‑1 and 8. A histogram of the distribution of Delta Over Baseline values from uninfected patients is shown in Figure 3.

Figure 3: Distribution of Data for Uninfected Patients as Determined in an Initial Clinical Study

Delta Over Baseline values, as determined by the original BreathID® in a pivotal clinical study, were used to confirm the initial clinical data. In the pre-therapy phase, there were 47 infected and 253 uninfected patients. Congruent results obtained by rapid urease test and histological examinations of biopsy tissue were used as the reference standard and were confirmed by the original BreathID® in the 47 infected patients. In the post therapy phase, 22 patients were infected and 50 were uninfected. The reference standard in this phase was at least one positive finding from either an endoscopic test (rapid urease or histology) or by a UBT.

The following values were obtained for the data from the pivotal study:

Upper 97.5% percentile of the Negative patients: 2.245

Lower 2.5% percentile of the Positive patients: 7.212

A histogram of the distribution of Delta Over Baseline values from pre- therapy uninfected (first phase) patients is shown in Figure 4.

Figure 4: Distribution of Data for Pre-Therapy Uninfected Patients as Determined in the Pivotal Study

SECTION 13. PERFORMANCE CHARACTERISTICS

13.1. VALIDATION OF IDKIT HP® TWO BREATH SAMPLE BAGS

Experimental Design

A multi-center, non-randomized, open label, validation, pivotal study, designed to confirm the efficacy of the IDkit Hp® Two as part of the BreathID® Hp Lab System was performed for initial diagnosis and post eradication testing using the same 5 DOB diagnostic cut-off versus composite biopsy results (histology and RUT or culture). Patients were asked to perform the urea breath test using two pairs of breath sample bags from the IDkit Hp® Two. The sample analysis was performed either on site or in a remote location using a BreathID® Hp Lab System. Each pair of breath sample bags was analyzed at a different time point up to 14 days apart in order to assess the stability of the breath samples in the breath sample bags. At 11 United States clinical sites and 2 sites in Israel, 196 adult initial diagnosis patients and 76 post–therapy patients who were positive for infection and who had completed eradication therapy at least six weeks prior to participation in the study were recruited. Patients were evaluated by at least 3 diagnostic methods:

1. Histopathology: Biopsy specimens, fixed with formalin, were cut into sections, stained with at least H&E and IHC stains, and examined by an experienced pathologist at a central laboratory.

2. Rapid Urease Test (RUT): Biopsy specimens were tested for urease activity with an FDA-cleared test according to the instructions in its package insert.

3. BreathID® Hp Lab test: The BreathID® Hp Lab test was performed in accordance with the procedures described in the IDkit Hp® Two package insert.

Results

The results are presented in two-way contingency tables. The exact binomial distribution was used to calculate the lower and upper limits of the 95% confidence intervals of the performance statistic.

Pre-Therapy

In Table 1, the BreathID® Hp Lab System using IDkit Hp® Two outcome is compared to composite results from the two endoscopy biopsy-based methods (rapid urease test and histological exam) for initial diagnosis. Table 2 and Table 3 compare the BreathID® Hp Lab test using IDkit Hp® Two to rapid urease tests (RUT) and histological exams, respectively.

Table 1: Comparison of the BreathID® Hp Lab Test using IDkit Hp® Two to Composite Reference Method (RUT and histological exam) Pre-Therapy

 | BreathID Hp Lab test using IDkit Hp Two
Composite Reference Method* | Positive | Negative | Total
Positive | 37 | 0 | 37
Negative | 3 | 139 | 142
Total | 40 | 139 | 179

*H. pylori positive is defined as positive rapid urea test and positive histology.

H. pylori negative is defined as negative rapid urea test and negative histology.

Sensitivity: 100% [95% CI (90.60; 100.00)]

Specificity: 97.9% [95% CI (93.97; 99.28)]

Table 2: Comparison of the BreathID® Hp Lab Test using IDkit Hp® Two to Rapid Urease Test (RUT) Pre-Therapy

 | BreathID Hp Lab test using IDkit Hp Two
RUT | Positive | Negative | Total
Positive | 37 | 5 | 42
Negative | 7 | 140 | 147
Total | 44 | 145 | 189

Percent Positive Agreement: 88.1% [95% CI (75.00; 94.81)]

Percent Negative Agreement: 95.2% [95% CI (90.50; 97.67)]

Table 3: Comparison of the BreathID® Hp Lab Test using IDkit Hp® Two to Histology Pre-Therapy

 | BreathID Hp Lab test using IDkit Hp Two
Histology | Positive | Negative | Total
Positive | 41 | 1 | 42
Negative | 3 | 144 | 147
Total | 44 | 145 | 189

Percent Positive Agreement: 97.6% [95% CI (87.68; 99.58)]

Percent Negative Agreement: 98.0% [95% CI (94.17; 99.30)]

Post Therapy

Table 4 compares the BreathID® Hp Lab Test using IDkit Hp® Two to Composite Reference Method (rapid urease test and histological exam) in patients after they completed the eradication therapy. Table 5 and Table 6 compare the BreathID® Hp Lab test using IDkit Hp® Two to rapid urease tests (RUT) and histological exams, respectively.

Table 4: Comparison of the BreathID® Hp Lab Test using IDkit Hp® Two to Composite Reference Method Post-Therapy

 | BreathID Hp Lab test using IDkit Hp Two
Composite Reference Method* | Positive | Negative | Total
Positive | 12 | 1 | 13
Negative | 0 | 55 | 55
Total | 12 | 56 | 68

* H. pylori positive is defined as positive RUT or positive Histology

H. pylori negative is defined as negative RUT and negative Histology

Sensitivity: 92.3% [95% CI (66.69; 98.63)]

Specificity: 100% [95% CI (93.47; 100.00)]

Table 5: Comparison of the BreathID® Hp Lab Test using IDkit Hp® Two to RUT Post-Therapy

 | BreathID Hp Lab test using IDkit Hp Two
RUT | Positive | Negative | Total
Positive | 11 | 0 | 11
Negative | 1 | 56 | 57
Total | 12 | 56 | 68

Percent Positive Agreement: 100% [95% CI (74.12; 100)]

Percent Negative Agreement: 98.25% [95% CI 90.71; 99.69)]

Table 6: Comparison of the BreathID® Hp Lab Test using IDkit Hp® Two to Histology Post-Therapy

 | BreathID Hp Lab test using IDkit Hp Two
Histology | Positive | Negative | Total
Positive | 12 | 1 | 13
Negative | 0 | 55 | 55
Total | 12 | 56 | 68

Percent Positive Agreement: 92.3% [95% CI (66.69; 98.63)]

Percent Negative Agreement: 100% [95% CI (93.47; 100)]

13.2. CONFIRMATORY STUDY OF IDKIT HP® TWO IN THE PEDIATRIC POPULATION

Experimental Design

A multi-center, non-randomized, open label study was conducted with the primary goal of confirming the safety of the 13C-urea substrate in pediatric subjects, and a secondary goal of evaluating performance of the BreathID® Hp Lab System with IDkit Hp® Two breath sample bags in pediatric subjects aged 3-17 years using the same 5 DOB diagnostic cut-off, in this population compared to stool antigen testing. A central lab analyzed the stool specimens. The study was conducted at 6 clinical sites where the sites were geographically diverse, differing in size and diverse in experience representing both point of care testing as well as sites utilizing a clinical laboratory. Local site personnel were trained on administering the breath test. To represent point of care and clinical laboratory settings, the sample analysis was performed either on site or at a central laboratory using a BreathID® Hp Lab System.

Results

A total number of 54 subjects were screened, 1 subject was a screening failure prior to any study related procedure. Fifty-three subjects were enrolled and followed for safety assessment, 42 of which completed the full study protocol requirements with evaluable endpoints. There were no reportable major safety concerns due to adverse events. Table 7 presents the diagnosis as assessed by the BreathID® Hp Lab System using IDkit Hp® Two breath sample bags compared to the assessment by an FDA cleared H. pylori stool antigen test.

Table 7: Comparison of the BreathID® Hp Lab Test using IDkit Hp® Two to an FDA-cleared H. pylori stool antigen test

 | BreathID Hp Lab test using IDkit Hp Two
Stool antigen results | Positive | Negative | Total
Positive | 14 | 1 | 15
Negative | 0 | 27 | 27
Total | 14 | 28 | 42

Percent Positive Agreement: 93.3% [95% CI (68.05; 99.83)]

Percent Negative Agreement: 100% [95% CI (87.23; 100)]

13.3. STABILITY OF BREATH SAMPLES OVER TIME

193 initial diagnosis patients were asked to perform the urea breath test using two sets of IDkit Hp® Two. The sample analysis was performed either on site or in a remote location using a BreathID® Hp Lab System. Each pair of breath sample bags was analyzed at a different time point up to 14 days apart in order to assess the stability of the breath samples in the bags. There were 191 subjects with two evaluable results for analysis. Out of 45 samples positive on the first measurement, 44 remained positive on the second measurement (Percent Positive Agreement: 97.8% [95% CI (88.43, 99.61)]). Out of 146 samples negative on the first measurement, all 146 remained negative on the second measurement (Percent Negative Agreement: 100% [95% CI (97.44, 100)]).

13.4. REPRODUCIBILITY AND REPEATABILITY RESULTS

Separate analytical studies were conducted to evaluate the reproducibility and precision (repeatability) of results when measurements are made with the BreathID® Hp Lab System or by the BreathID® Smart System by different technicians and/or using different systems, or when testing is done on different days and at different sites, and on samples that are stored up to 14 days at different temperature and humidity conditions.

13.5. REPRODUCIBILITY ANALYTICAL STUDY FOR THE BREATHID® HP LAB SYSTEM

Three different accurate gas isotope pairs were used with Delta Over Baseline (DOB) values of 3.3, 6.4, and 15.5 in a bench study. Two operators were asked to operate each of three BreathID® Hp Lab System at three different sites for five days, in order to measure the DOB values for samples from each of the three batches. The results demonstrated that the standard deviation and overall reproducibility were stable over different batches for both the operator, the devices and between days. The reproducibility standard deviation was 0.65 or less for all batches, and the between days, devices and operators standard deviation was 0.66 or less in all cases, which is less than the natural variability of the DOB measurement. Table 8 summarizes the results of the Reproducibility Analytical Study.

Table 8: Results of Reproducibility Analytical Study for the BreathID® Hp Lab System

Expected DOB | Parameter | SD Value | 95% CI | CV
DOB: 3.3‰ | Reproducibility | 0.53 | [0.46 - 0.63] | 14.8%
DOB: 3.3‰ | Between Days Precision | 0.54 | [0.46 - 0.60] | 14.9%
DOB: 3.3‰ | Between Devices Precision | 0.54 | [0.45 - 0.59] | 14.9%
DOB: 3.3‰ | Between Operators Precision | 0.53 | [0.44 - 0.58] | 14.8%
DOB: 6.4‰ | Reproducibility | 0.60 | [0.52 - 0.71] | 9.7%
DOB: 6.4‰ | Between Days Precision | 0.62 | [0.54 - 0.68] | 10.0%
DOB: 6.4‰ | Between Devices Precision | 0.60 | [0.51 - 0.65] | 9.7%
DOB: 6.4‰ | Between Operators Precision | 0.60 | [0.51 - 0.70] | 9.7%
DOB: 15.5‰ | Reproducibility | 0.65 | [0.57 - 0.77] | 4.3%
DOB: 15.5‰ | Between Days Precision | 0.65 | [0.56 - 0.72] | 4.3%
DOB: 15.5‰ | Between Devices Precision | 0.66 | [0.56 - 0.73] | 4.4%
DOB: 15.5‰ | Between Operators Precision | 0.65 | [0.55 - 0.76] | 4.3%

13.6. REPRODUCIBILITY ANALYTICAL STUDY FOR BREATHID® SMART SYSTEM

Three different accurate gas isotope pairs were used with Delta Over Baseline (DOB) values of 3.3, 6.4, and 15.5 in a bench study. Three BreathID® Smart Systems were used for five days, in order to measure the DOB values for samples from each of the three batches. The results demonstrated that the standard deviation and overall reproducibility were stable over different batches. The reproducibility standard deviation was 0.55 or less for all batches, and the between days and devices standard deviation was 0.18 or less in all cases, which is less than the natural variability of the DOB measurement. Table 9 summarizes the results of the Reproducibility Analytical Study.

Table 9: Results of Reproducibility Analytical Study for the BreathID® Smart System

Expected DOB | Parameter | SDValue | 95% CI | CV
DOB: 3.3‰ | Reproducibility | 0.55 | [0.46 - 0.68] | 16.4%
DOB: 3.3‰ | Between Days Precision | 0.16 | - | 4.8%
DOB: 3.3‰ | Between Devices Precision | 0.18 | - | 5.5%
DOB: 6.4‰ | Reproducibility | 0.50 | [0.43 - 0.62] | 8.8%
DOB: 6.4‰ | Between Days Precision | 0.18 | - | 3.1%
DOB: 6.4‰ | Between Devices Precision | 0.14 | -- | 2.5%
DOB: 15.5‰ | Reproducibility | 0.55 | [0.47 - 0.65] | 3.7%
DOB: 15.5‰ | Between Days Precision | 0.00 | - | 0.0%
DOB: 15.5‰ | Between Devices Precision | 0.14 | - | 1.0%

13.7. PRECISION ANALYTICAL STUDY (REPEATABILITY) FOR THE BREATHID® HP LAB SYSTEM

Three different accurate gas isotope pairs were used with Delta Over Baseline (DOB) values of 3.3, 6.4, and 15.5 in a bench study. The DOB values for samples from each of the three batches were measured on the BreathID® Hp Lab System twice a day for 12 days. The results demonstrated that the standard deviation and overall repeatability were stable over different batches and different days. The repeatability standard deviation was 0.64 or less and the overall between days standard deviation was 0.72 or less, which is less than the natural variability of the DOB measurement. Table 10 summarizes the results of the Precision Analytical Study.

Table 10: Results of the Precision Analytical Study for the BreathID® Hp Lab System

Expected DOB | Parameter | SD Value | 95% CI | CV
DOB: 3.3‰ | Repeatability | 0.56 | [0.44 - 0.78] | 16.9%
 | Between Days Precision | 0.63 | [0.52 - 0.80] | 17.4%
DOB: 6.4‰ | Repeatability | 0.59 | [0.46 - 0.82] | 9.2%
 | Between Days Precision | 0.68 | [0.56 - 0.87] | 10.6%
DOB: 15.5‰ | Repeatability | 0.64 | [0.50 - 0.89] | 4.3%
 | Between Days Precision | 0.72 | [0.60 - 0.92] | 4.8%

13.8. PRECISION ANALYTICAL STUDY (REPEATABILITY) FOR BREATHID® SMART SYSTEM

Three different accurate gas isotope pairs were used with Delta Over Baseline (DOB) values of 3.3, 6.4, and 15.5 in a bench study. The DOB values for samples from each of the three batches were measured on the BreathID® Smart System for 20 days. The results demonstrated that the standard deviation and overall repeatability were stable over different batches and different days. The repeatability standard deviation was 0.62 or less and the between days standard deviation was 0.26 or less, which is less than the natural variability of the DOB measurement. Table 11 summarizes the results of the Precision Analytical Study.

Table 11: Results of the Precision Analytical Study for the BreathID® Smart System

Expected DOB | Parameter | SDValue | 95% CI | CV
DOB: 3.3‰ | Repeatability | 0.62 | [0.50 - 0.79] | 17.0%
DOB: 3.3‰ | Between Days Precision | 0.15 | [0.00 - 0.47] | 4.0%
DOB: 6.4‰ | Repeatability | 0.48 | [0.39 - 0.61] | 7.9%
DOB: 6.4‰ | Between Days Precision | 0.24 | [0.00 - 0.50] | 3.9%
DOB: 15.5‰ | Repeatability | 0.64 | [0.47 - 0.75] | 3.9%
DOB: 15.5‰ | Between Days Precision | 0.72 | [0.00 - 0.57] | 1.7 %

13.9 BAGS STORAGE ANALYTICAL STUDY

One accurate gas isotope pair with Delta Over Baseline (DOB) value of 3.3 was used in a bench study. Breath sample bags were stored at two different storage conditions representing the two extreme temperatures of the recommended storage range, 15°C and 35°C, and at the high limit of the recommended relative humidity (RH), 70%. The DOB values for samples from each storage condition were measured on the BreathID® Hp Lab System 7 times during 14 consecutive days for each storage condition, on days 2, 4, 8, 9, 10, 11 and 14. The results demonstrated that the standard deviation and overall repeatability were stable over different batches, different days and different storage conditions. The overall repeatability standard deviation and the between days precision standard deviation were 0.60 or less, which is less than the natural variability of the DOB measurement. Table 12 summarizes the results of the Bags Storage Analytical Study.

Table 12: Results of the Bags Storage Analytical Study per Storage Condition

Expected DOB | Storage Condition | Parameter | SD Value | 95% CI | CV
DOB: 3.3‰ | 15°C | Overall Repeatability | 0.57 | [0.45 - 0.78] | 15.0%
DOB: 3.3‰ | 15°C | Between Days Precision | 0.57 | [0.45 - 0.68] | 15.0%
DOB: 3.3‰ | 35°C + RH 70% | Overall Repeatability | 0.60 | [0.48 - 0.82] | 16.9%
DOB: 3.3‰ | 35°C + RH 70% | Between Days Precision | 0.60 | [0.47 - 0.72] | 16.9%

SECTION 14. BIBLIOGRAPHY

1. Marshall BJ, Warren JR. Unidentified curved bacilli on gastric epithelium in active chronic gastritis. Lancet 1983;1:1273–5.
2. Suerbaum S, Michetti P. Helicobacter pylori infection. N Engl J Med 2002;347:1175-86.
3. Dominguez-Munoz JE, Leodolter A, Sauerbruch T, et al. A citric acid solution is an optimal test drink in the 13C-urea breath test for the diagnosis of Helicobacter pylori infection. Gut 1997;40:459–62.
4. Leodolter A, Dominguez-Munoz JE, Von Armim U, et al. 13C-urea breath test for the diagnosis of Helicobacter pylori infection. A further simplification for clinical practice. Scand J Gastroenterol 1998;33:267–70.
5. Graham DY, Runke D, Anderson S, et al. Citric acid as the test meal for the 13C-urea breath test. Am J Gastroenterol 1999;94:1214–7.
6. Borriello SP, Reed PJ, Dolby JM, et al. Microbial and metabolic profile of achlorhydric stomach: comparison of pernicious anaemia and hypogammaglobulinaemia. J Clin Pathol 1985;38:946-53.

This publication, in whole or in part, may not be reproduced, disclosed, translated into any language or computer language or distributed without the prior written consent of Meridian Bioscience Israel Ltd.

Manufactured by:

Meridian Bioscience Israel Ltd.

4 Ha’Maayan St. Modiin, Israel 7177872

Tel: +972-8-9737500

Fax: +972-8-9737501

e-mail:modiin.contact@meridiabioscience.com

USA Distributor:

Meridian Bioscience Inc.

3471 River Hills Drive

Cincinnati, OH 45244, USA

Tel: 1-800-543-1980

www.meridianbioscience.com/breathid

Part Number: MLD01016 Revision: 07 Issued: July 2022